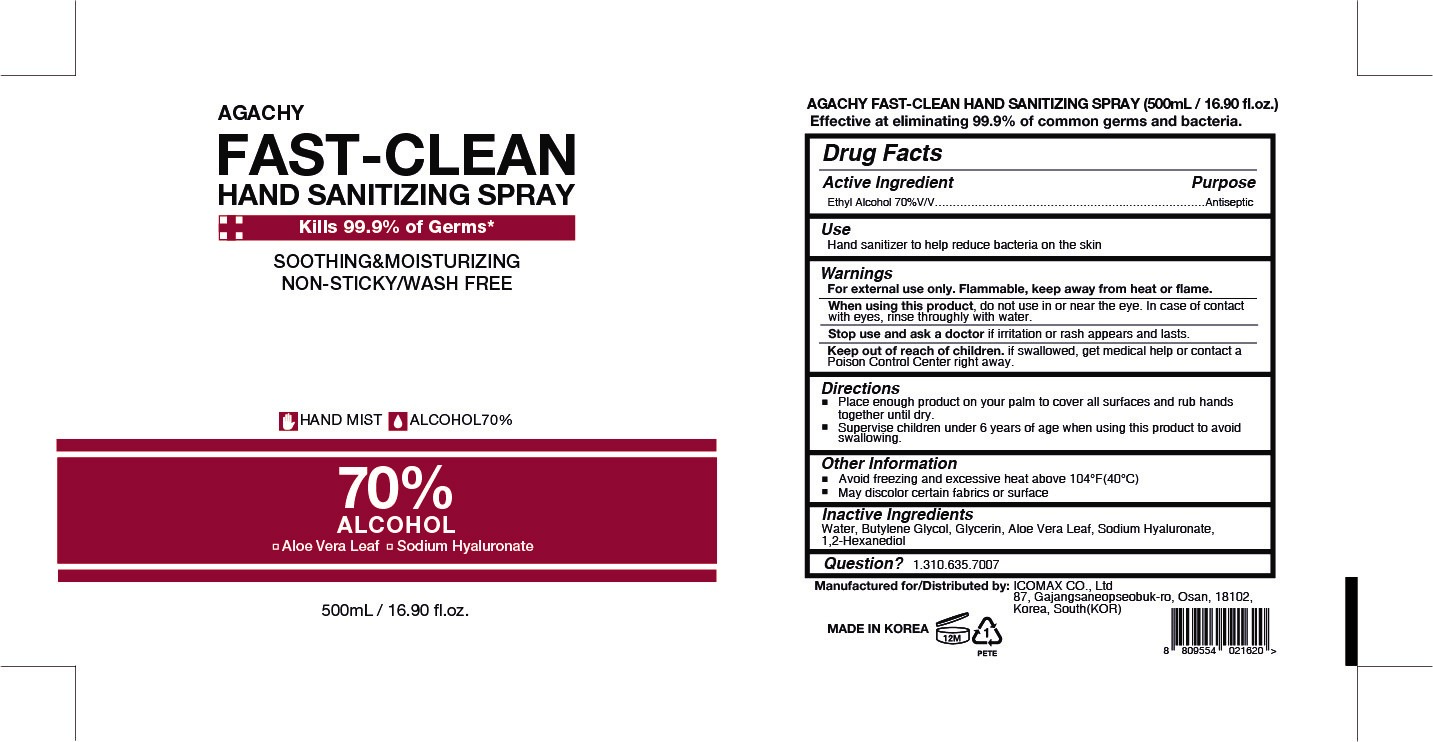 DRUG LABEL: AGACHY FAST CLEAN HAND SANITIZINGSPRAY
NDC: 77201-004 | Form: SPRAY
Manufacturer: ICOMAX Co., Ltd.
Category: otc | Type: HUMAN OTC DRUG LABEL
Date: 20200707

ACTIVE INGREDIENTS: ALCOHOL 70 mL/100 mL
INACTIVE INGREDIENTS: HYALURONATE SODIUM; 1,2-HEXANEDIOL; GLYCERIN; BUTYLENE GLYCOL; WATER; ALOE VERA LEAF

Active Ingredient

Ethyl Alcohol 70% v/v

Purpose

Antiseptic

Use

Hand Sanitizer to help reduce bacteria on the skin.

Warnings

For external use only. Flammable. Keep away from heat or flame.

When using this product do not use in or near the eye. In case of contact with eyes, rinse thoroughly with water.

Stop use and ask a doctor if irritation or rash appears and lasts.

Keep out of reach of children. If swallowed, get medical help or contact a Poison Control Center right away.

Directions

- Place enough product on your palm to cover all surfaces and rub hands together until dry.
- Supervise children under 6 years of age when using this product to avoid swallowing.

Other information

- Avoid freezing and excessive heat above 104°F(40°C)
- May discolor certain fabrics or surface

Inactive ingredients

Water, Butylene Glycol, Glycerin, Aloe Vera Leaf, Sodium Hyaluronate, 1,2-Hexanediol